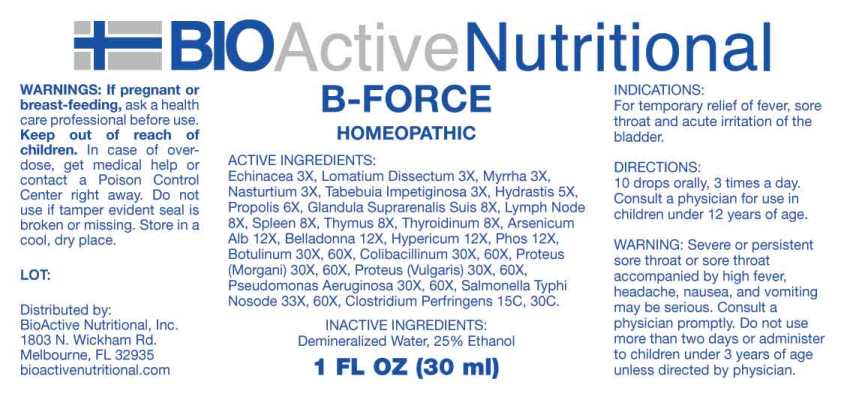 DRUG LABEL: B Force
NDC: 43857-0576 | Form: LIQUID
Manufacturer: BioActive Nutritional, Inc.
Category: homeopathic | Type: HUMAN OTC DRUG LABEL
Date: 20240305

ACTIVE INGREDIENTS: ECHINACEA ANGUSTIFOLIA WHOLE 3 [hp_X]/1 mL; LOMATIUM DISSECTUM ROOT 3 [hp_X]/1 mL; MYRRH 3 [hp_X]/1 mL; NASTURTIUM OFFICINALE 3 [hp_X]/1 mL; HANDROANTHUS IMPETIGINOSUS BARK 3 [hp_X]/1 mL; GOLDENSEAL 5 [hp_X]/1 mL; PROPOLIS WAX 6 [hp_X]/1 mL; SUS SCROFA ADRENAL GLAND 8 [hp_X]/1 mL; SUS SCROFA LYMPH 8 [hp_X]/1 mL; SUS SCROFA SPLEEN 8 [hp_X]/1 mL; SUS SCROFA THYMUS 8 [hp_X]/1 mL; SUS SCROFA THYROID 8 [hp_X]/1 mL; ARSENIC TRIOXIDE 12 [hp_X]/1 mL; ATROPA BELLADONNA 12 [hp_X]/1 mL; HYPERICUM PERFORATUM WHOLE 12 [hp_X]/1 mL; PHOSPHORUS 12 [hp_X]/1 mL; BOTULINUM TOXIN TYPE A 30 [hp_X]/1 mL; ESCHERICHIA COLI 30 [hp_X]/1 mL; PROTEUS VULGARIS 30 [hp_X]/1 mL; PSEUDOMONAS AERUGINOSA 30 [hp_X]/1 mL; PROTEUS MORGANII 30 [hp_X]/1 mL; SALMONELLA ENTERICA SUBSP. ENTERICA SEROVAR TYPHI 33 [hp_X]/1 mL; CLOSTRIDIUM PERFRINGENS 15 [hp_C]/1 mL
INACTIVE INGREDIENTS: WATER; ALCOHOL

DRUG FACTS:

ACTIVE INGREDIENTS:

Echinacea Angustifolia 3X, Lomatium Dissectum 3X, Myrrha 3X, Nasturtium Aquaticum 3X, Tabebuia Impetiginosa 3X, Hydrastis Canadensis 5X, Propolis 6X, Glandula Suprarenalis Suis 8X, Lymph Node (Suis) 8X, Spleen (Suis) 8X, Thymus (Suis) 8X, Thyroidinum (Suis) 8X, Arsenicum Album 12X, Belladonna 12X, Hypericum Perforatum 12X, Phosphorus 12X, Botulinum 30X, 60X, Colibacillinum Cum Natrum Muriaticum 30X, 30X, Proteus (Vulgaris) 30X, 60X, Pseudomonas Aeruginosa 30X, 60X, Proteus (Morgani) 30X, 60X, Salmonella Typhi Nosode 33X, 60X, Clostridium Perfringens 15C, 30C.

INDICATIONS:

For temporary relief of fever, sore throat and acute irritation of the bladder.

WARNINGS:

If pregnant or breast-feeding, ask a health care professional before use.

Keep out of reach of children. In case of overdose, get medical help or contact a Poison Control Center right away.

Do not use if tamper evident seal is broken or missing.

Store in a cool, dry place.

Warning: Severe or persistent sore throat or sore throat accompanied by high fever, headache, nausea, and vomiting may be serious. Consult a physician promptly. Do not use more than two days or administer to children under 3 years of age unless directed by physician.

Keep out of reach of children. In case of overdose, get medical help or contact a Poison Control Center right away.

DIRECTIONS:

10 drops orally, 3 times a day. Consult a physician for use in children under 12 years of age.

INDICATIONS:

For temporary relief of fever, sore throat and acute irritation of the bladder.

INACTIVE INGREDIENTS:

Demineralized Water, 25% Ethanol

QUESTIONS:

Distributed by:

BioActive Nutritional, Inc.

1803 N. Wickham Rd.

Melbourne, FL 32935

bioactivenutritional.com

PACKAGE LABEL DISPLAY:

BIOActive Nutritional

B-FORCE

HOMEOPATHIC

1 FL OZ (30 ml)